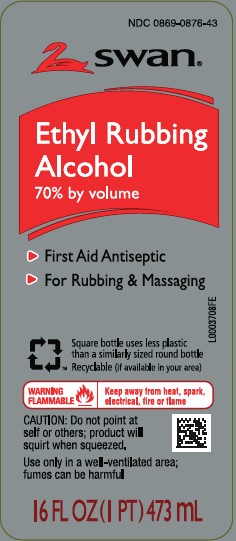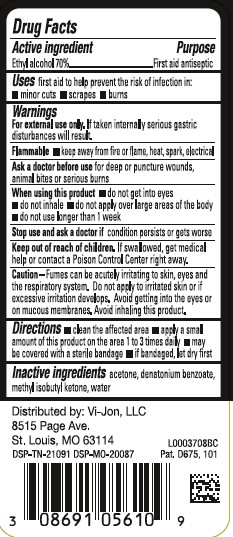 DRUG LABEL: Rubbing
NDC: 0869-0876 | Form: LIQUID
Manufacturer: Consumer Product Partners, LLC
Category: otc | Type: HUMAN OTC DRUG LABEL
Date: 20250701

ACTIVE INGREDIENTS: ALCOHOL 70 mL/100 mL
INACTIVE INGREDIENTS: ACETONE; DENATONIUM BENZOATE; METHYL ISOBUTYL KETONE; WATER

Swan 876.002/876AC
70% Ethyl Rubbing Alcohol

Active Ingredient

Ethyl alcohol 70%

Purpose

First aid antiseptic

Uses

first aid to help prevent the risk of infection in:

- minor cuts
- scrapes
- burns

Warnings

For external use only. If taken internally serious gastric disturbances will result.

Flammable

keep away from fire or flame, heat, spark, electrical

Ask a doctor before use

for deep or puncture wounds, animal bites or serious burns

When using this product

- do not get into eyes
- do not inhale
- do not apply over large areas of the body
- do not use longer than 1 week

Stop use and ask a doctor if

condition persists or gets worse

Keep out of reach of children.

If swallowed, get medical help or contact a Poison Control Center right away.

Caution

Fumes can be acutely irriting to skin, eyes ad the respiratory system. Do not apply to irritated skin or if excessive irritation develops. Avoid getting into the eyes or on mucous membranes. Avoid inhaling this product.

Directions

- clean the affected area
- apply a small amount of this product on the affected area 1 to 3 times daily
- may be covered with a sterile bandage
- if bandaged, let dry first

Inactive ingredients

acetone, denatonium benzoate, methyl isobutyl ketone, water

Adverse reaction

Distributed by: Vi-Jon, LLC

8515 Page Ave.

St. Louis, MO 63114

DSP-TN-21091 DSP-MO-20087

Pat. D675, 101

principal display panel

NDC 0869-0876-43

swan®

Ethyl Rubbing Alcohol

70% by volume

- First Aid Antiseptic
- For Rubbing & Massaging

Square bottle uses less plastic than a similarly sized round bottle

Recyclable (if available in your area)

WARNING FLAMMABLE - Keep away from heat, spark, electrical, fire or flame

CAUTION: DO not point at self or others; product will squirt when squeezed.

Use only in well-ventilated area; fumes can be harmful.

16 FL OZ (1 PT) 473 mL